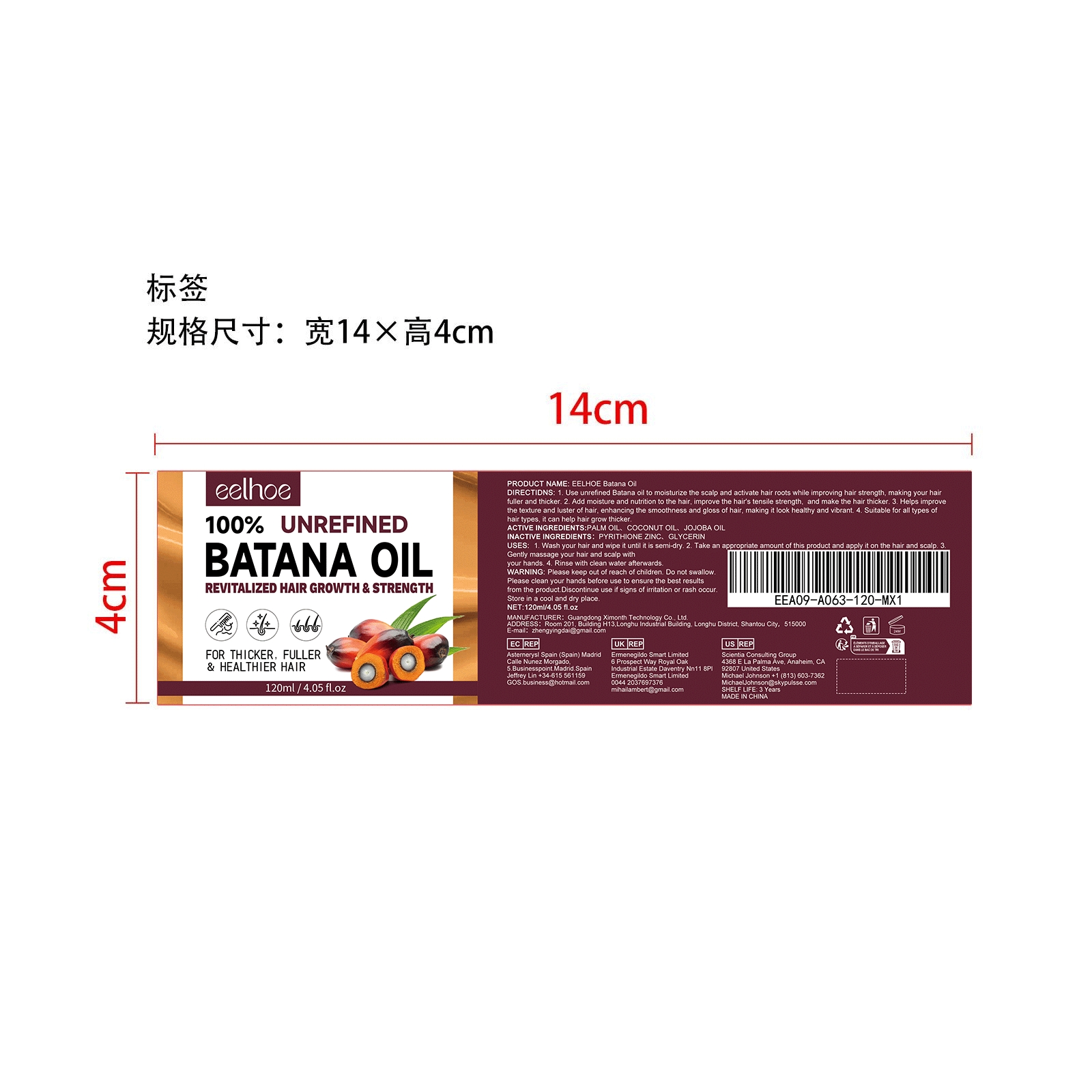 DRUG LABEL: EELHOE Batana Oil
NDC: 84660-047 | Form: CREAM
Manufacturer: Guangdong Ximonth Technology Co., Ltd.
Category: otc | Type: HUMAN OTC DRUG LABEL
Date: 20241019

ACTIVE INGREDIENTS: JOJOBA OIL 36 mg/120 mg; COCONUT OIL 18 mg/120 mg; PALM OIL 36 mg/120 mg
INACTIVE INGREDIENTS: PYRITHIONE ZINC 12 mg/120 mg; GLYCERIN 18 mg/120 mg

ACTIVE INGREDIENTS

PALM OIL、COCONUT OIL、JOJOBA OIL

PURPOSE

1. Use unrefined Batana oil to moisturize the scalp and activate hair roots while improving hair strength, making your hair fuller and thicker.

2. Add moisture and nutrition to the hair, improve the hair's tensile strength, and make the hair thicker.

3. Helps improve the texture and luster of hair, enhancing the smoothness and gloss of hair, making it look healthy and vibrant.

4. Suitable for all types of hair types, it can help hair grow thicker.

USE

1. Wash your hair and wipe it until it is semi-dry.

2. Take an appropriate amount of this product and apply it on the hair and scalp.

3. Gently massage your hair and scalp with
your hands.

4. Rinse with clean water afterwards.

WARNINGS

Please keep out of reach of children. Do not swallow. Please clean your hands before use to ensure the best results from the product. Discontinue use if signs of irritation or rash occur. Store in a cool and dry place.

Do not use

Please keep out of reach of children. Do not swallow.

Stop Use

Discontinue use if signs of irritation or rash occur.

KEEP OUT OF REACH OF CHILDREN

Please keep out of reach of children. Do not swallow.

STORAGE AND HANDLING

Store in a cool and dry place.

INACTIVE INGREDIENT

PYRITHIONE ZINC、GLYCERIN